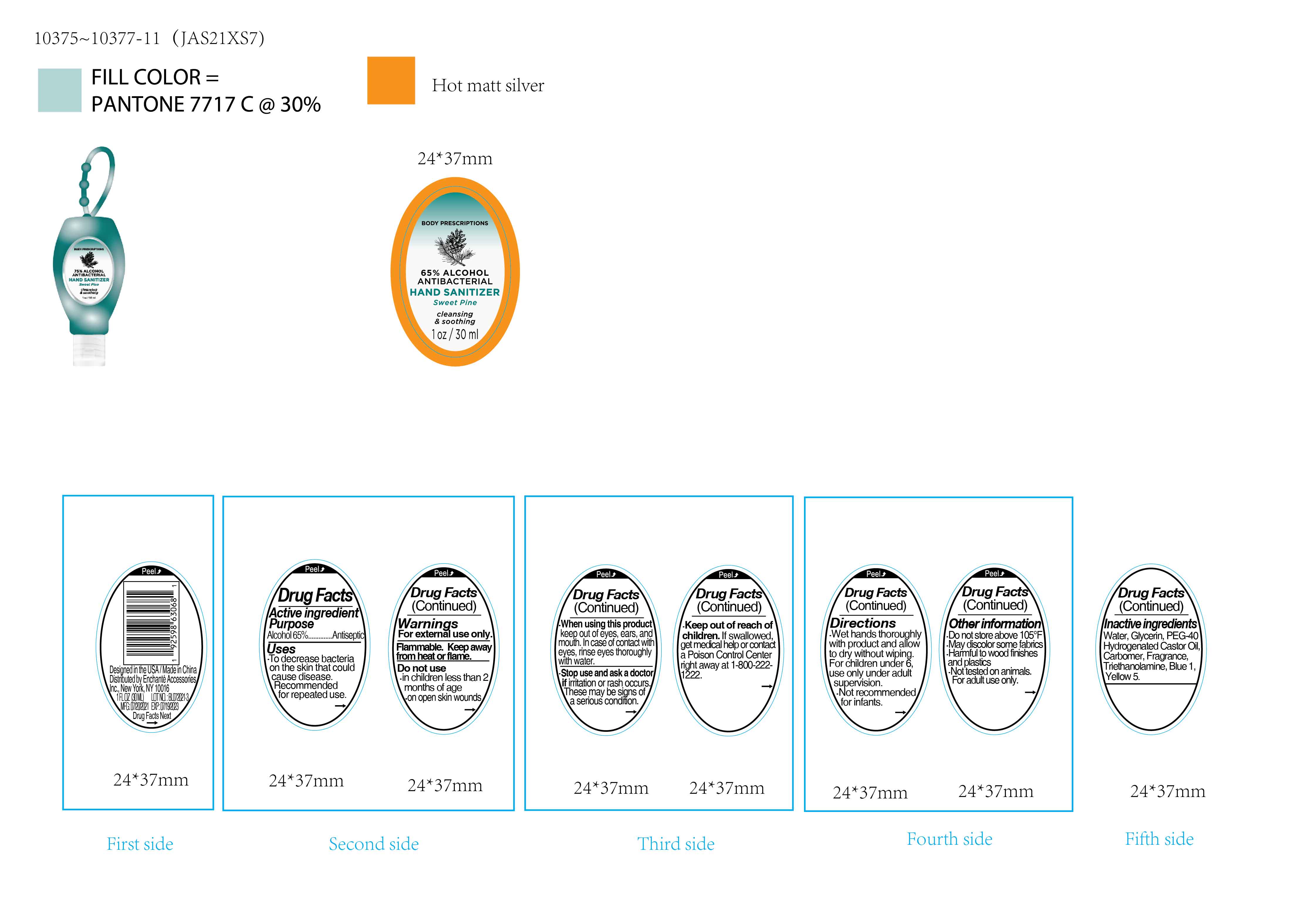 DRUG LABEL: BODY PRESCRIPTIONS 65 PERCENT ALCOHOL ANTIBACTERIAL HAND SANITIZER Sweet Pine
NDC: 50563-463 | Form: SOLUTION
Manufacturer: ENCHANTE ACCESSORIES INC.
Category: otc | Type: HUMAN OTC DRUG LABEL
Date: 20210704

ACTIVE INGREDIENTS: ALCOHOL 65 mL/100 mL
INACTIVE INGREDIENTS: TROLAMINE; WATER; GLYCERIN; CARBOMER 940; POLYOXYL 40 HYDROGENATED CASTOR OIL; FD&C YELLOW NO. 5; FD&C BLUE NO. 1

50563-463 / JAS21XS7

Active Ingredient

Alcohol: 65% (v/v)

Purpose

Antiseptic

Use

■ To decrease bacteria on the skin that could cause disease
■Recommended for repeated use

WARNINGS

For external use only

Flammable. Keep away from heat or flame

Do not use

in children less than two months of age

on open skin wounds

When using this product, keep out of eyes, ears, and mouth
In case of contact with eyes, rinse eyes thoroughly with water

Stop Use

Stop use and ask a doctor if irritation or rash occurs. These may be signs of a serious condition

Keep out of reach of children. If swallowed, get medical help or contact a poison control center right away at 1-800-222-1222

Directions

Wet hands thoroughly with product and allow to dry without wiping

For children under 6, use only under adult supervision

Not recommended for infants

Other information

Do not store above 105F

May discolor some fabrics

Harmful to wood finishes and plastics

Not tested on animals

For adult use only

Inactive ingredients

Water, Glycerin, PEG-40 Hydrogenated Castor Oil, Carbomer, Fragrance, Triethanolamine, Blue 1, Yellow 5